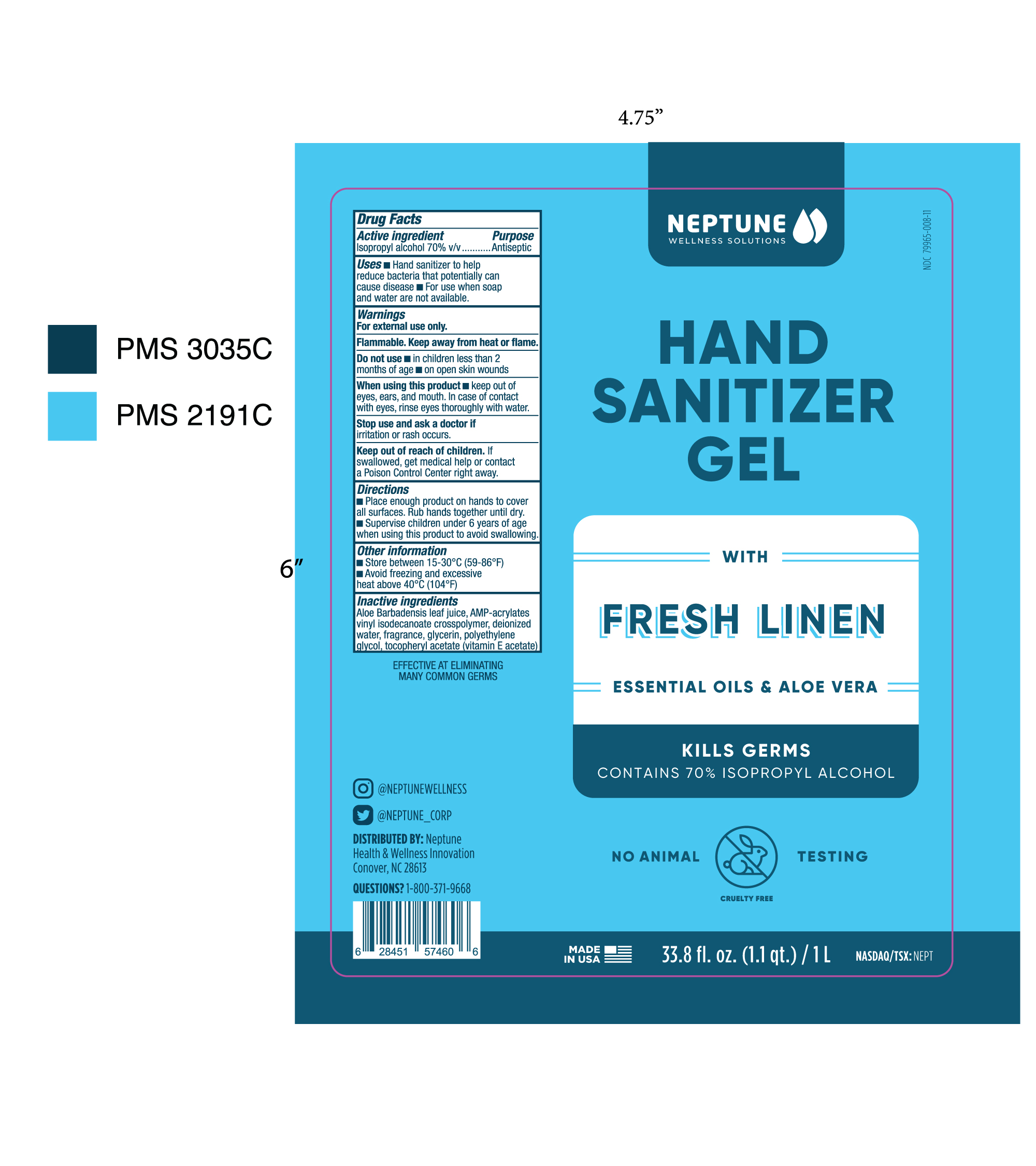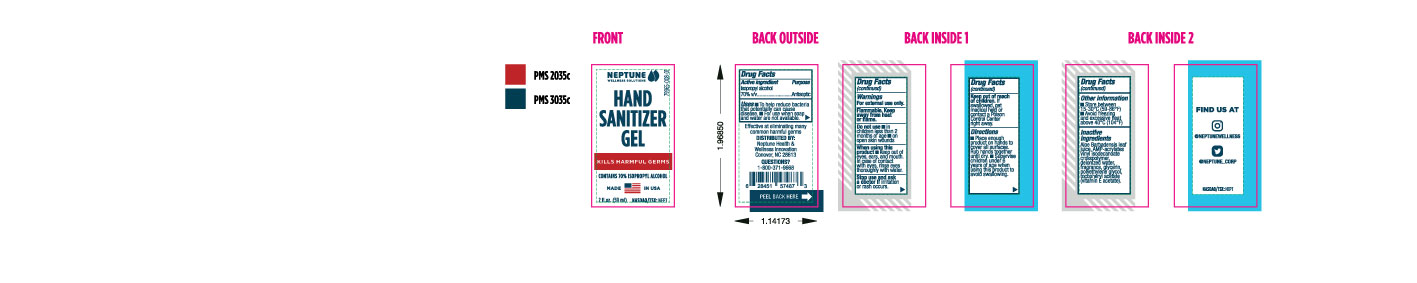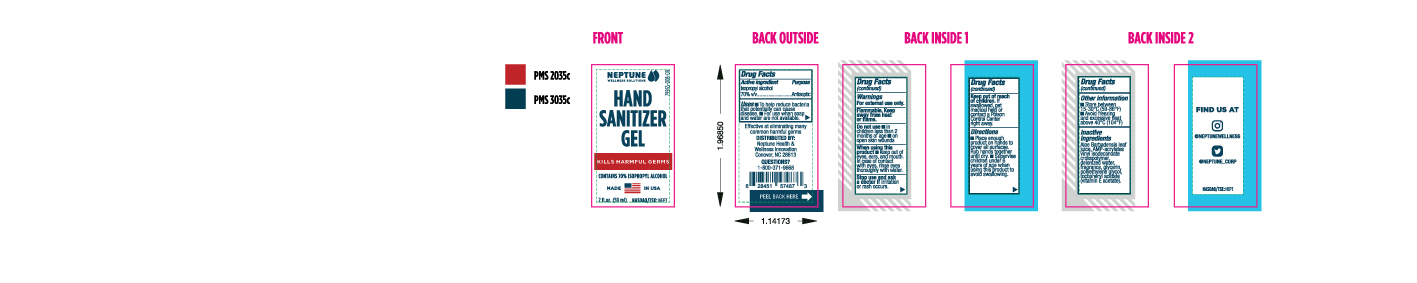 DRUG LABEL: Hand Sanitizer
NDC: 79965-008 | Form: GEL
Manufacturer: Neptune Health & Wellness Innovation, Inc.
Category: otc | Type: HUMAN OTC DRUG LABEL
Date: 20200909

ACTIVE INGREDIENTS: ISOPROPYL ALCOHOL 70 mL/100 mL
INACTIVE INGREDIENTS: .ALPHA.-TOCOPHEROL ACETATE, DL- 0.1 mL/100 mL; ALOE VERA LEAF 0.3 mL/100 mL; ACRYLATES/VINYL ISODECANOATE CROSSPOLYMER (10000 MPA.S NEUTRALIZED AT 0.5%) 0.3 mL/100 mL; GLYCERIN 0.5 mL/100 mL; POLYETHYLENE GLYCOL, UNSPECIFIED 1.7 mL/100 mL; WATER 26.8 mL/100 mL

Active Ingredient(s)

Isopropyl Alcohol 70% v/v. Purpose: Antiseptic

Purpose

Antiseptic, Hand Sanitizer

Use

Hand Sanitizer to help reduce bacteria that potentially can cause disease. For use when soap and water are not available.

Warnings

For external use only. Flammable. Keep away from heat or flame

Do not use

- in children less than 2 months of age
- on open skin wounds

When using this product keep out of eyes, ears, and mouth. In case of contact with eyes, rinse eyes thoroughly with water.
Stop use and ask a doctor if irritation or rash occurs. These may be signs of a serious condition.
Keep out of reach of children. If swallowed, get medical help or contact a Poison Control Center right away.

Stop use and ask a doctor if irritation or rash occurs. These may be signs of a serious condition.

Keep out of reach of children. If swallowed, get medical help or contact a Poison Control Center right away.

Directions

- Place enough product on hands to cover all surfaces. Rub hands together until dry.
- Supervise children under 6 years of age when using this product to avoid swallowing.

Other information

- Store between 15-30C (59-86F)
- Avoid freezing and excessive heat above 40C (104F)

Inactive ingredients

Aloe Barbadensis leaf juice, AMP-acrylates vinyl isodecanoate crosspolymer, deionized water, fragrance, glycerin, polyethylene glycol, tocopheryl acetate (vitamin E acetate).

Package Label - Principal Display Panel

2 fl. oz. (60 ml) NDC: 79965-008-00

2 fl. oz. (60 ml) NDC: 79965-008-01

33.8 fl. oz. (1.1 qt.) / 1 L NDC: 79965-008-11